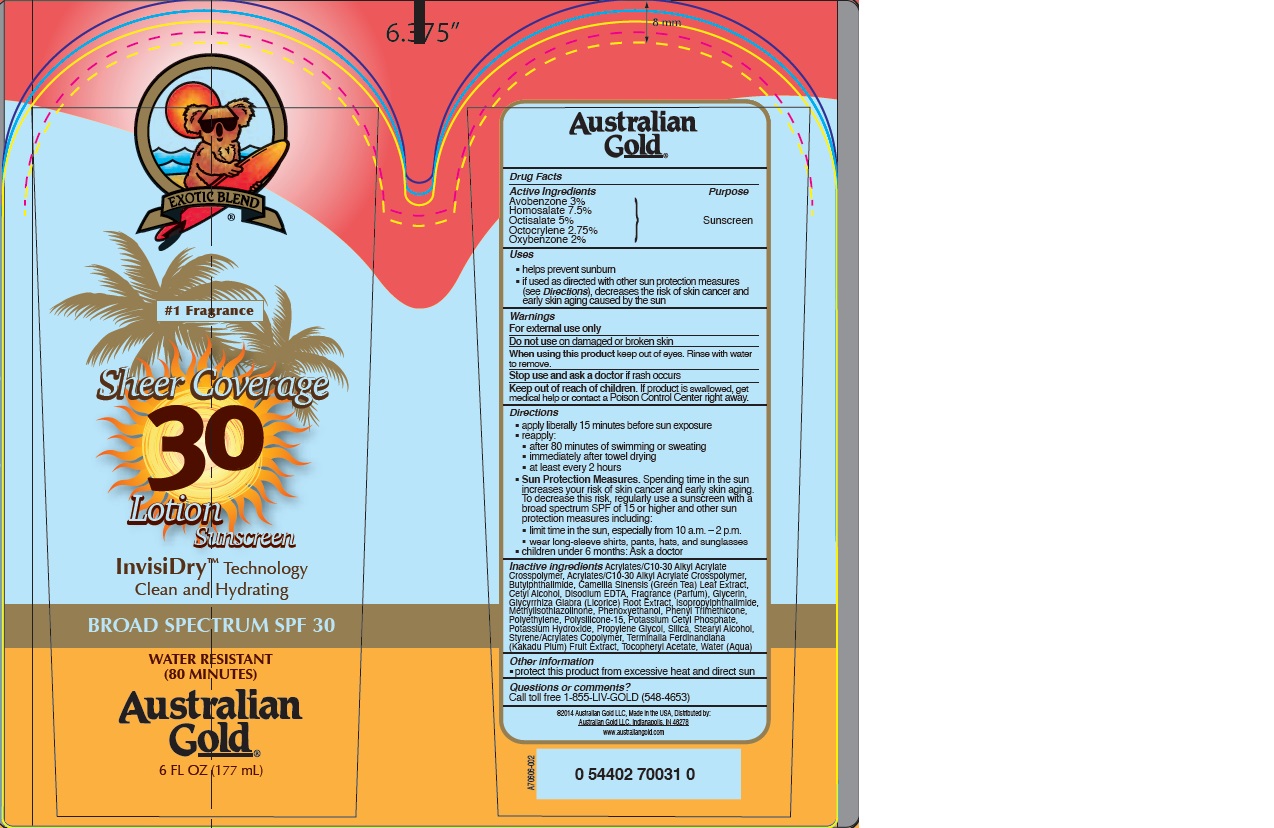 DRUG LABEL: Australian Gold
NDC: 58443-0203 | Form: LOTION
Manufacturer: Prime Enterprises Inc.
Category: otc | Type: HUMAN OTC DRUG LABEL
Date: 20200117

ACTIVE INGREDIENTS: OXYBENZONE 20.4 mg/1 mL; AVOBENZONE 30.6 mg/1 mL; HOMOSALATE 76.5 mg/1 mL; OCTISALATE 51 mg/1 mL; OCTOCRYLENE 28.1 mg/1 mL
INACTIVE INGREDIENTS: GLYCERIN; STEARYL ALCOHOL; STYRENE/ACRYLAMIDE COPOLYMER (MW 500000); KAKADU PLUM; SILICON DIOXIDE; POTASSIUM HYDROXIDE; GREEN TEA LEAF; EDETATE DISODIUM; PHENYL TRIMETHICONE; METHYLISOTHIAZOLINONE; PHENOXYETHANOL; HIGH DENSITY POLYETHYLENE; POLYSILICONE-15; POTASSIUM CETYL PHOSPHATE; PROPYLENE GLYCOL; (C10-C30)ALKYL METHACRYLATE ESTER; CETYL ALCOHOL; N-BUTYLPHTHALIMIDE; LICORICE; ALPHA-TOCOPHEROL ACETATE; ISOPROPYLPHTHALIMIDE; WATER

Australian Gold Broad Spectrum SPF 30 Sheer Sunscreen

Active Ingredients

Avobenzone 3%

Homosalate 7.5%

Octisalate 5%

Octocrylene 2.75%

Oxybenzone 2%

Purpose

Sunscreen

Uses

- helps prevent sunburn
- if used as directed with other sun protection measures (see Directions), decreases the risk of skin cancer and early skin aging caused by the sun

WARNINGS

For external use only.

Do not use on damaged or broken skin

When using this product keep out of eyes. Rinse with water to remove.

Stop use and ask a doctor if rash occurs

Keep out of reach of children. If product is swallowed, get medical help or contact a Poison Control Center right away.

Directions

- apply liberally 15 minutes before sun exposure
- reapply:
- after 80 minutes of swimming or sweating
- immediately after towel drying
- at least every 2 hours
- Sun Protection Measures. Spending time in the sun increases your risk of skin cancer and early skin aging. To decrease this risk, regularly use a sunscreen with broad spectrum SPF of 15 or higher and other sun protection measures including:
- limit time in the sun, especially from 10 a.m. – 2 p.m.
- wear long-sleeve shirts, pants, hats, and sunglasses
- children under 6 months: Ask a doctor

INACTIVE INGREDIENT

Acrylates/C10-30 Alkyl Acrylate Crosspolymer, Butylphthalimide, Camellia Sinensis (Green Tea) Leaf Extract, Cetyl Alcohol, Disodium EDTA, Fragrance (Parfum), Glycerin, Glycyrrhiza Glabra (Licorice) Root Extract, Isopropylphthalimide, Methylisothiazolinone, Phenoxyethanol, Phenyl Trimethicone, Polyethylene, Polysilicone-15, Potassium Cetyl Phosphate, Potassium Hydroxide, Propylene Glycol, Silica, Stearyl Alcohol, Styrene/Acrylates Copolymer, Terminalia Ferdinandiana (Kakadu Plum) Fruit Extract, Tocopheryl Acetate, Water (Aqua)

Other Information

- protect this product from excesive heat and direct sun

Questions or Comments?

Call toll free 1-855-LIV-GOLD (548-4653)